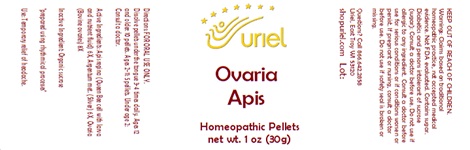 DRUG LABEL: Ovaria Apis
NDC: 48951-7099 | Form: PELLET
Manufacturer: Uriel Pharmacy Inc.
Category: homeopathic | Type: HUMAN OTC DRUG LABEL
Date: 20240403

ACTIVE INGREDIENTS: ROYAL JELLY 6 [hp_X]/1 1; SILVER 6 [hp_X]/1 1; BOS TAURUS OVARY 8 [hp_X]/1 1
INACTIVE INGREDIENTS: SUCROSE

Ovaria Apis

INDICATIONS AND USAGE

Directions: FOR ORAL USE ONLY.

DOSAGE AND ADMINISTRATION

Dissolve pellets under the tongue 3-4 times daily. Ages 12 and older: 10 pellets. Ages 2-11: 5 pellets. Under age 2: Consult a doctor.

ACTIVE INGREDIENT

Active Ingredients: Apis regina (Queen Bee cell with larva and nutrient fluid) 6X, Argentum met. (Silver) 6X, Ovaria (Bovine ovaries) 8X

Inactive Ingredients: Organic sucrose

prepared using rhythmical processes

PURPOSE

Use: Temporary relief of headache.

KEEP OUT OF REACH OF CHILDREN.

WARNINGS

Warnings: Claims based on traditional homeopathic practice, not accepted medical evidence. Not FDA evaluated. Contains sugar. Diabetics and persons intolerant of sucrose (sugar): Consult a doctor before use. Do not use if allergic to any ingredient. Consult a doctor before use for serious conditions or if conditions worsen or persist. If pregnant or nursing, consult a doctor before use. Do not use if safety seal is broken or missing.

QUESTIONS

Questions? Call 866.642.2858 Uriel, East Troy WI 53120 shopuriel.com Lot: